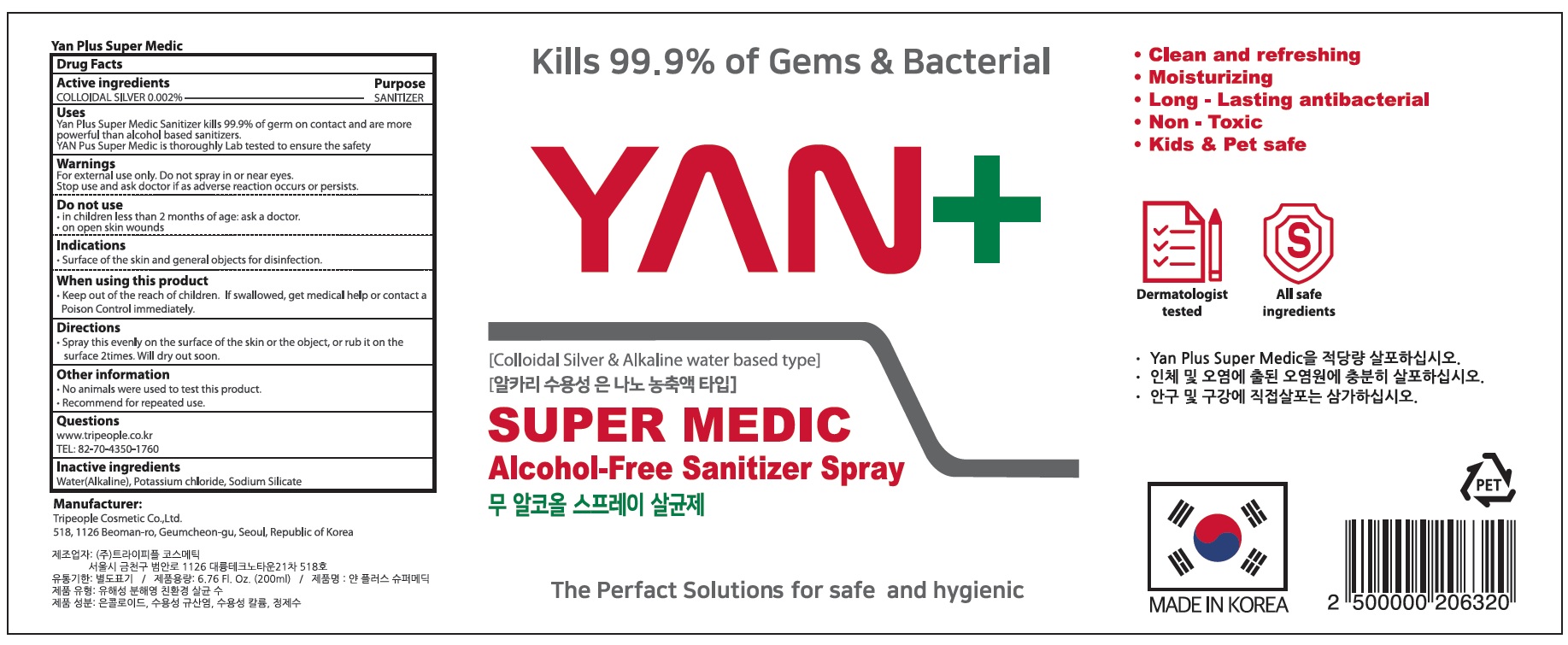 DRUG LABEL: Yan Plus Super Medic
NDC: 76642-010 | Form: SPRAY
Manufacturer: TRIPEOPLE COSMETIC CO.,LTD.
Category: otc | Type: HUMAN OTC DRUG LABEL
Date: 20200509

ACTIVE INGREDIENTS: SILVER 0.004 g/200 mL
INACTIVE INGREDIENTS: Water; Potassium chloride; SODIUM SILICATE

ACTIVE INGREDIENT

Active ingredients
COLLOIDAL SILVER 0.002%

INACTIVE INGREDIENT

Inactive ingredients
Water(Alkaline), Potassium chloride, Sodium Silicate

PURPOSE

Purpose: SANITIZER

WARNINGS

For external use only. Do not spray in or near eyes.
Stop use and ask doctor if as adverse reaction occurs or persists.
--------------------------------------------------------------------------------------------------------
Do not use
• in children less than 2 months of age: ask a doctor.
• on open skin wounds
--------------------------------------------------------------------------------------------------------
Indications
.Surface of the skin and general objects for disinfection.
--------------------------------------------------------------------------------------------------------
When using this product
Keep out of the reach of children. If swallowed, get medical help or contact a Poison Control immediately.

KEEP OUT OF REACH OF CHILDREN

If swallowed, get medical help or contact a Poison Control immediately.

Uses

Yan Plus Super Medic Sanitizer kills 99.9% of germ on contact and are more powerful than alcohol based sanitizers.
YAN Pus Super Medic is thoroughly Lab tested to ensure the safety

Directions

• Spray this evenly on the surface of the skin or the object, or rub it on the surface 2times. Will dry out soon.

Other information

• No animals were used to test this product.
• Recommend for repeated use.

QUESTIONS

www.tripeople.co.kr
TEL: 82-70-4350-1760